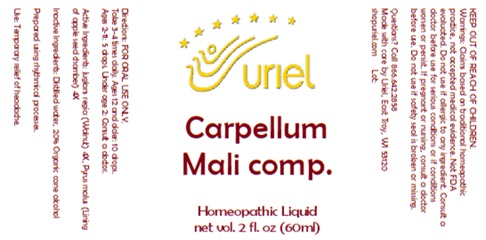 DRUG LABEL: Carpellum Mali Comp.
NDC: 48951-3034 | Form: LIQUID
Manufacturer: Uriel Pharmacy Inc.
Category: homeopathic | Type: HUMAN OTC DRUG LABEL
Date: 20250801

ACTIVE INGREDIENTS: ENGLISH WALNUT 4 [hp_X]/1 mL; MALUS DOMESTICA WHOLE 4 [hp_X]/1 mL
INACTIVE INGREDIENTS: WATER; ALCOHOL

Carpellum Mali Comp.

DOSAGE AND ADMINISTRATION

Take 3-4 times daily. Ages 12 and older: 10 drops. Ages 2-11: 5 drops. Under age 2: Consult a doctor.

ACTIVE INGREDIENT

Active Ingredients: Juglans regia (Walnut) 4X, Pyrus malus (Lining of apple seed chamber) 4X

Inactive Ingredients: Distilled water, Organic cane alcohol

Prepared using rhythmical processes.

PURPOSE

Use: Temporary relief of headache.

KEEP OUT OF REACH OF CHILDREN.

WARNINGS

Warnings: Claims based on traditional homeopathic practice, not accepted medical evidence. Not FDA evaluated. Do not use if allergic to any ingredient. Consult a doctor before use for serious conditions or if conditions worsen or persist. If pregnant or nursing, consult a doctor before use. Do not use if safety seal is broken or missing.

Questions? Call 866.642.2858
Made with care by Uriel, East Troy, WI 53120
shopuriel.com Lot: